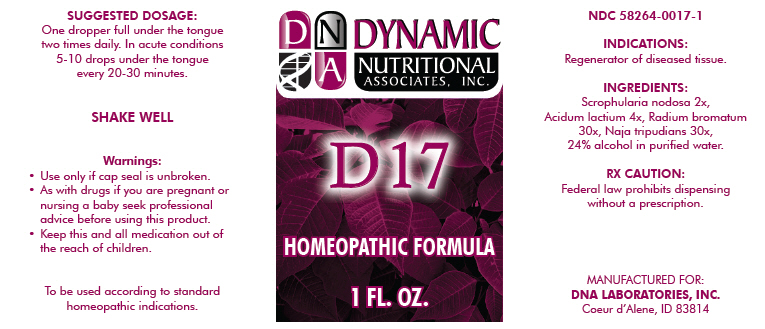 DRUG LABEL: D17
NDC: 58264-0017 | Form: SOLUTION
Manufacturer: DNA Labs, Inc.
Category: homeopathic | Type: HUMAN OTC DRUG LABEL
Date: 20250113

ACTIVE INGREDIENTS: NAJA NAJA WHOLE 30 [hp_X]/1 mL; SCROPHULARIA NODOSA 2 [hp_X]/1 mL; LACTIC ACID, DL- 4 [hp_X]/1 mL; RADIUM BROMIDE 30 [hp_X]/1 mL
INACTIVE INGREDIENTS: ALCOHOL; WATER

D-17

NDC 58264-0017-1

INDICATIONS

PURPOSE

Regenerator of diseased tissue.

ACTIVE INGREDIENT

INGREDIENTS

Scrophularia nodosa 2x, Acidum lactium 4x, Radium bromatum 30x, Naja tripudians 30x, 24% alcohol in purified water.

RX CAUTION

Federal law prohibits dispensing without a prescription.

SUGGESTED DOSAGE

One dropper full under the tongue two times daily. In acute conditions 5-10 drops under the tongue every 20-30 minutes.

STORAGE AND HANDLING

SHAKE WELL

Warnings

- Use only if cap seal is unbroken.

PREGNANCY OR BREAST FEEDING

- As with drugs if you are pregnant or nursing a baby seek professional advice before using this product.

KEEP OUT OF REACH OF CHILDREN

- Keep this and all medication out of the reach of children.

To be used according to standard homeopathic indications.

PRINCIPAL DISPLAY PANEL - 1 FL. OZ. Bottle Label

DYNAMIC
NUTRITIONAL
ASSOCIATES, INC.

D 17

HOMEOPATHIC FORMULA

1 FL. OZ.